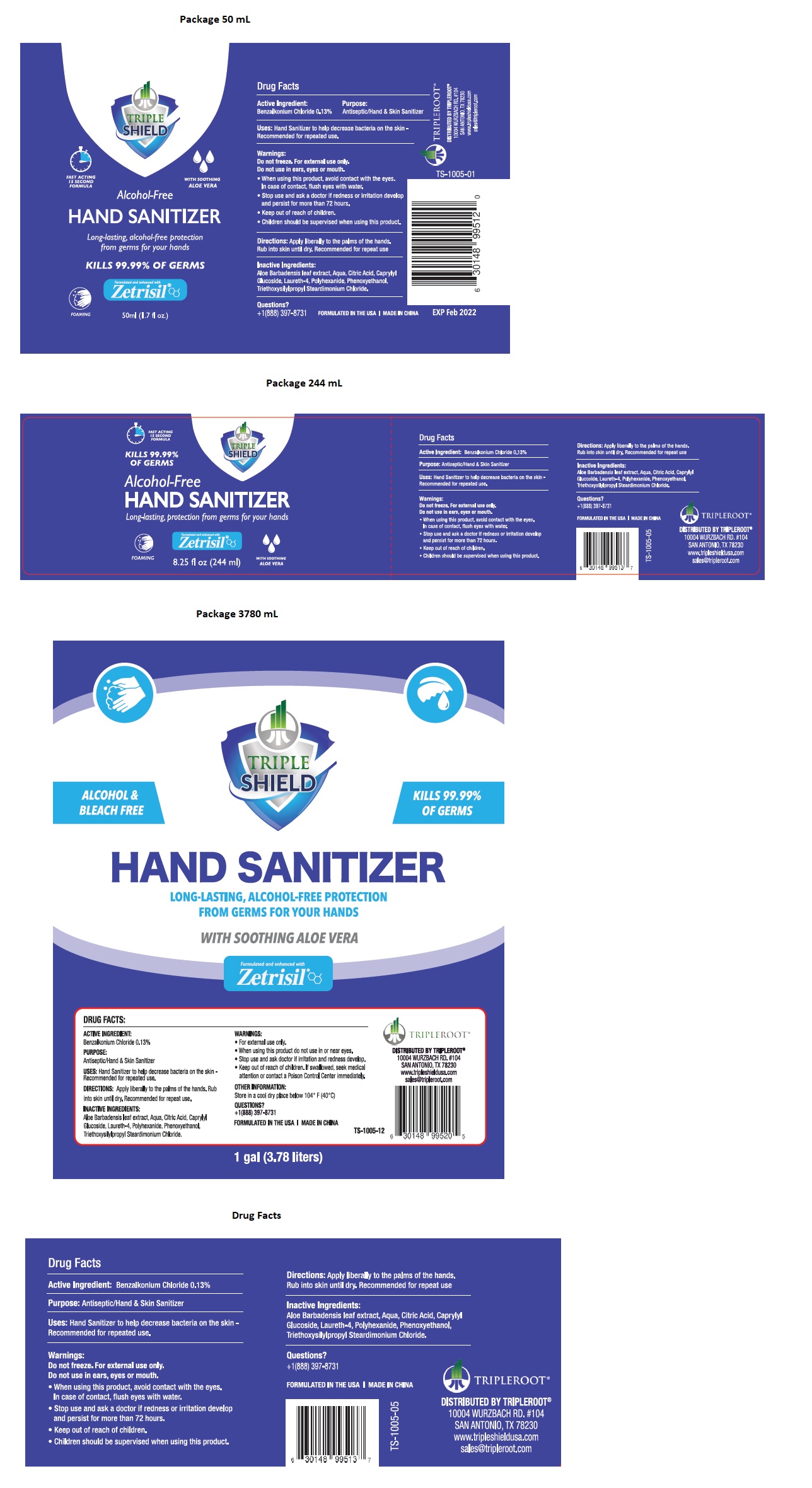 DRUG LABEL: TRIPLE SHIELD HAND SANITIZER
NDC: 71884-032 | Form: LIQUID
Manufacturer: Enviro Specialty Chemicals Inc
Category: otc | Type: HUMAN OTC DRUG LABEL
Date: 20211209

ACTIVE INGREDIENTS: BENZALKONIUM CHLORIDE 0.13 g/100 mL
INACTIVE INGREDIENTS: ALOE VERA LEAF; WATER; CITRIC ACID MONOHYDRATE; CAPRYLYL GLUCOSIDE; LAURETH-4; POLIHEXANIDE; PHENOXYETHANOL; TRIETHOXYSILYLPROPYL STEARDIMONIUM CHLORIDE

TRIPLE SHIELD Alcohol-Free HAND SANITIZER

Active Ingredient:

Benzalkonium Chloride 0.13%

Purpose:

Antiseptic/Hand & Skin Sanitizer

INDICATIONS AND USAGE

Uses: Hand Sanitizer to help decrease bacteria on the skin -

Recommended for repeated use.

Warnings:

Do not freeze. For external use only.

Do not use in ears, eyes or mouth.

• When using this product avoid contact with the eyes. In case of contact, flush eyes with water.

• Stop use and ask doctor if redness or irritation develop and persist for more than 72 hours.

- Keep out of reach of children.
- Children should be supervised when using this product.

DOSAGE AND ADMINISTRATION

Directions: Apply liberally to the palms of the hands. Rub into skin until dry. Recommended for repeat use.

Other Information:

Store in a cool dry place below 104˚F(40˚C)

Inactive Ingredients:

Aloe Barbadensis leaf extract, Aqua, Citric Acid, Caprylyl Glucoside, Laureth-4, Polyhexanide, Phenoxyethanol, Triethoxysilylpropyl

Steardimonium Chloride.

Questions?

+1(888) 397-8731

FAST ACTING

15 SECOND FORMULA

KILLS 99.99% OF GERMS

ALCOHOL & BLEACH FREE

Long-lasting, protection from germs for your hands

FOAMING

Formulated and enhanced with

Zetrisil

WITH SOOTHING ALOE VERA

FORMULATED IN THE USA | MADE IN CHINA

DISTRIBUTED BY TRIPLEROOT®

10004 WURZBACH RD.#104

SAN ANTONIO, TX 78230

www.tripleshieldusa.com

sales@tripleroot.com